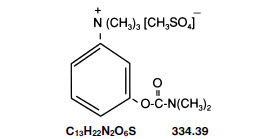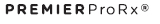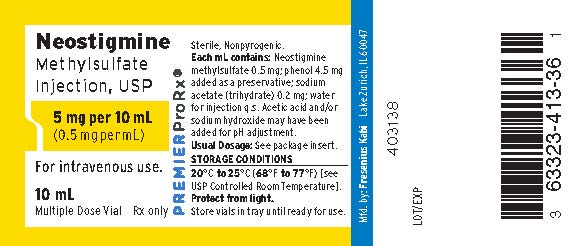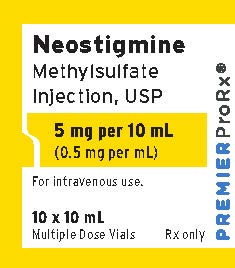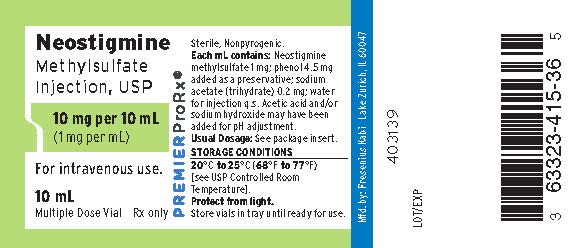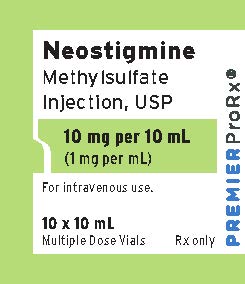 DRUG LABEL: Neostigmine Methylsulfate
NDC: 63323-413 | Form: INJECTION, SOLUTION
Manufacturer: Fresenius Kabi USA, LLC
Category: prescription | Type: HUMAN PRESCRIPTION DRUG LABEL
Date: 20241015

ACTIVE INGREDIENTS: NEOSTIGMINE METHYLSULFATE 0.5 mg/1 mL
INACTIVE INGREDIENTS: PHENOL 4.5 mg/1 mL; SODIUM ACETATE 0.2 mg/1 mL; ACETIC ACID; SODIUM HYDROXIDE

HIGHLIGHTS OF PRESCRIBING INFORMATION

These highlights do not include all the information needed to use NEOSTIGMINE METHYLSULFATE injection safely and effectively. See full prescribing information for NEOSTIGMINE METHYLSULFATE injection.
NEOSTIGMINE METHYLSULFATE injection, for intravenous use
Initial U.S. Approval: 1939

1 INDICATIONS AND USAGE

Neostigmine Methylsulfate, a cholinesterase inhibitor, is indicated for reversal of the effects of nondepolarizing neuromuscular blocking agents (NMBA) after surgery (1).

2 DOSAGE AND ADMINISTRATION

Dosage

- Should be administered by trained healthcare providers (2.1)
- Recommend use of a peripheral nerve stimulator to determine whether neostigmine methylsulfate should be administered and to monitor recovery from neuromuscular blockade (2.1).
- Recommended dosage range is 0.03 mg/kg to 0.07 mg/kg for reversing non-depolarizing neuromuscular block when administered with an anticholinergic agent (atropine or glycopyrrolate) (2.2, 2.3, 2.4)
  - For reversal of NMBAs with shorter half-lives, when first twitch response is substantially greater than 10% of baseline, or when a second twitch is present: 0.03 mg/kg by intravenous route (2.2)
  - For reversal of NMBAs with longer half-lives or when first twitch response is close to 10% of baseline: 0.07 mg/kg by intravenous route (2.2)
- Maximum total dosage is 0.07 mg/kg or up to a total of 5 mg (whichever is less) (2.2)
- An anticholinergic agent, e.g., atropine sulfate or glycopyrrolate, should be administered prior to or concomitantly with neostigmine methylsulfate (2.4)

Dose of Anticholinergic Agent (atropine or glycopyrrolate)

- Administer atropine sulfate (~15 mcg/kg) or glycopyrrolate (~10 mcg/kg) intravenously either several minutes before or concomitantly with neostigmine methylsulfate (using separate syringes) (2.4)

3 DOSAGE FORMS AND STRENGTHS

Injection: 0.5 mg/mL and 1 mg/mL solution in 10 mL multiple dose vial in packages of 10 vials (3)

4 CONTRAINDICATIONS

- Hypersensitivity to neostigmine (4)
- Peritonitis or mechanical obstruction of urinary or intestinal tracts (4)

5 WARNINGS AND PRECAUTIONS

- Bradycardia: Atropine or glycopyrrolate should be administered prior to administration of neostigmine methylsulfate injection to lessen risk of bradycardia (5.1)
- Coexisting Conditions: Patients with known cardiac disease, cardiac arrhythmias, or recent coronary artery occlusion may be particularly sensitive to the hemodynamic effects of neostigmine; their blood pressure and electrocardiogram should be continuously monitored with the initiation of neostigmine treatment and for a duration sufficient to assure hemodynamic stability. (5.2)
- Neuromuscular Dysfunction: Can occur if large doses of neostigmine methylsulfate are administered when there is minimal neuromuscular blockade; reduce the dose if recovery from neuromuscular blockade is nearly complete. (5.4)

6 ADVERSE REACTIONS

The most common adverse reactions include bradycardia and nausea and vomiting. (6)

To report SUSPECTED ADVERSE REACTIONS, contact Fresenius Kabi, Vigilance & Medical Affairs at 1-800-551-7176 or FDA at 1-800-FDA-1088 or www.fda.gov/medwatch.

8 USE IN SPECIFIC POPULATIONS

Pregnancy: No human data and limited animal exist. Use only if clearly needed.

FULL PRESCRIBING INFORMATION

1 INDICATIONS AND USAGE

Neostigmine Methylsulfate Injection, a cholinesterase inhibitor, is indicated for reversal of the effects of nondepolarizing neuromuscular blocking agents (NMBA) after surgery.

2 DOSAGE AND ADMINISTRATION

2.1 Important Dosage and Administration Instructions

- Neostigmine should be administered by trained healthcare providers familiar with the use, actions, characteristics, and complications of neuromuscular blocking agents (NMBA) and neuromuscular block reversal agents.
- Prior to Neostigmine Methylsulfate Injection administration and up until complete recovery of normal ventilation, the patient should be well ventilated and a patent airway maintained.
- Use a peripheral nerve stimulator capable of delivering a train-of-four (TOF) stimulus to evaluate the extent of recovery of neuromuscular function, and to determine the time of the first dose and the need for additional doses of Neostigmine Methylsulfate Injection.
- Prior to the administration of Neostigmine Methylsulfate Injection, there must be a twitch response to the first stimulus in the TOF of at least 10% of its baseline level (i.e., the response prior to NMBA administration).
- Dose selection should be based on the extent of spontaneous recovery at time of injection, half-life of the neuromuscular blocking agent (NMBA) to be reversed, and need for rapid NMBA reversal.
- Patients should continue to be monitored for adequacy of reversal of the effect of NMBAs for a period of time that would assure full recovery based on the patient’s medical condition and the pharmacokinetics of neostigmine and the NMBA used.
- Neostigmine Methylsulfate Injection is administered by intravenous bolus injection. Additional, carefully adjusted bolus doses are administered according to the patient’s response.
- An anticholinergic agent (e.g., atropine or glycopyrrolate) should be administered prior to or concomitantly with Neostigmine Methylsulfate Injection [ see Dosage and Administration (2.4), Warnings and Precautions (5.5) ].
- TOF monitoring alone should not be relied upon to determine the adequacy of reversal of neuromuscular blockade. Satisfactory recovery should be judged by the patient’s ability to maintain a patent airway, adequacy of ventilation, and skeletal muscle tone.

2.2 Recommended Dosage in Adults

- The recommended dose range of Neostigmine Methylsulfate Injection is 0.03 mg/kg to 0.07 mg/kg administered as an intravenous bolus.
- A dose less than 0.04 mg/kg is recommended for reversal of the effect of NMBAs with shorter half-lives (e.g., rocuronium), or when the first twitch response to the TOF stimulus is substantially greater than 10% of baseline, or when a second twitch is present.
- A dose of 0.07 mg/kg is recommended for the reversal of the effect of NMBAs with longer half-lives (e.g., vecuronium or pancuronium), or when first twitch response is not substantially greater than 10% of baseline, or if there is need for more rapid recovery.
- Additional doses may be required. The recommended maximum total dose is 0.07 mg/kg or up to a total of 5 mg, whichever is less.

2.3 Recommended Dosage in Pediatric Patients, including Neonates

Adult guidelines should be followed when Neostigmine Methylsulfate Injection is administered to pediatric patients. Pediatric patients require Neostigmine Methylsulfate Injection doses similar to those for adult patients.

2.4 Concomitant or Pre-Administration of Anticholinergic Agents

An anticholinergic agent (e.g., atropine sulfate or glycopyrrolate) should be administered intravenously several minutes prior to or with Neostigmine Methylsulfate Injection administration using separate syringes. For bradycardic patients, the anticholinergic agent should be administered prior to Neostigmine Methylsulfate Injection.

3 DOSAGE FORMS AND STRENGTHS

Injection: 0.5 mg/mL and 1 mg/mL solution in 10 mL multiple-dose vials in package of 10 vials.

4 CONTRAINDICATIONS

Neostigmine is contraindicated in patients with:

- known hypersensitivity to neostigmine methylsulfate (known hypersensitivity reactions have included urticaria, angioedema, erythema multiforme, generalized rash, facial swelling, peripheral edema, pyrexia, flushing, hypotension, bronchospasm, bradycardia and anaphylaxis).
- peritonitis or mechanical obstruction of the urinary or intestinal tracts.

5 WARNINGS AND PRECAUTIONS

5.1 Bradycardia

Neostigmine has been associated with bradycardia. An anticholinergic agent, (e.g., atropine sulfate or glycopyrrolate) should be administered prior to Neostigmine Methylsulfate Injection administration to lessen the risk of bradycardia [ see Dosage and Administration (2.4) ].

5.2 Cardiovascular Complications

Cardiac arrhythmias, nonspecific electrocardiogram changes, cardiac arrest, syncope and hypotension have been reported with neostigmine methylsulfate. In patients with certain cardiovascular conditions such as coronary artery disease, cardiac arrhythmias or recent acute coronary syndrome, the risk of blood pressure and heart rate complications may be increased. Risk of these complications may also be increased in patients with myasthenia gravis. Standard antagonism with anticholinergics (e.g., atropine) is generally successful to mitigate the risk of cardiovascular complications.

5.3 Hypersensitivity (Anaphylaxis)

Hypersensitivity reactions including anaphylaxis have been reported with neostigmine. Ensure that appropriate medical support measures, including atropine, cardiopulmonary resuscitation equipment, and medications to treat anaphylaxis are readily available.

5.4 Neuromuscular Dysfunction

Neuromuscular dysfunction has been associated with administration of large doses of neostigmine when neuromuscular blockade is minimal. To mitigate the risk of neuromuscular dysfunction, consider reducing the dose of neostigmine if recovery from neuromuscular blockade is nearly complete.

5.5 Cholinergic Crisis

Overdosage of neostigmine may cause cholinesterase inhibitor toxicity or cholinergic crisis which may be difficult to differentiate from myasthenia crisis since both conditions present with similar symptoms. Both conditions result in extreme muscle weakness but require radically different treatments. Cholinergic crisis requires immediate withdrawal of all anticholinergic medication and immediate use of atropine [ see Overdosage (10) ].

6 ADVERSE REACTIONS

6.1 Clinical Trial Experience

Because clinical trials are conducted under widely varying conditions, adverse reaction rates observed in the clinical trials of a drug cannot be directly compared to rates in the clinical trials of another drug and may not reflect the rates observed in practice.

The following serious adverse reactions are described below and elsewhere in the labeling:

- Bradycardia [ see Warnings and Precautions (5.1) ]
- Cardiovascular Complications [ see Warnings and Precautions (5.2) ]
- Hypersensitivity (Anaphylaxis) [ see Warnings and Precautions (5.3) ]

Adverse reactions to neostigmine methylsulfate are most often attributable to exaggerated pharmacological effects, in particular, at muscarinic receptor sites. The use of an anticholinergic agent, e.g., atropine sulfate or glycopyrrolate, may prevent or mitigate these reactions.

Quantitative adverse event data are available from trials of neostigmine methylsulfate in which 200 adult patients were exposed to the product. Adverse reactions that occurred with an overall frequency of 1% or greater included the following:

Allergic: Allergic reactions and anaphylaxis.

Neurological: Dizziness, syncope, weakness, convulsions, loss of consciousness, drowsiness, headache, dysarthria, miosis and visual changes.

Cardiovascular: Cardiac arrhythmias including bradycardia, tachycardia, atrioventricular block and nodal rhythm, as well as cardiac arrest, and hypotension.

Respiratory: Increased oral, pharyngeal and bronchial secretions, dyspnea, respiratory depression, oxygen desaturation, respiratory arrest and bronchospasm.

Dermatologic: Diaphoresis, flushing, rash, pruritus, and urticaria.

Gastrointestinal: Dry mouth, nausea, emesis, flatulence and increased peristalsis.

Genitourinary: Increased urinary frequency.

Musculoskeletal: Muscle cramps and spasm, arthralgia.

Psychiatric: Insomnia.

General: Incision site complication, pharyngolaryngeal pain, procedural complication, procedural pain.

6.2 Post-Marketing Experience

The following adverse reactions have been identified during parenteral use of neostigmine methylsulfate. Because these reactions are reported voluntarily from a population of uncertain size, it is not always possible to reliably estimate their frequency or establish a causal relationship to drug exposure.

Allergic Disorders: Allergic reactions, anaphylaxis

Nervous System Disorders: Convulsions, drowsiness, dysarthria, fasciculation, loss of consciousness, miosis, visual changes

Cardiovascular Disorders: Cardiac arrest, cardiac arrhythmias (A-V block, nodal rhythm), hypotension, nonspecific EKG changes, syncope

Respiratory, Thoracic and Mediastinal Disorders: Bronchospasm; increased oral, pharyngeal and bronchial secretions; respiratory arrest; respiratory depression

Skin and Subcutaneous Tissue Disorders: Rash, urticaria diaphoresis, flushing

Gastrointestinal Disorders: Bowel cramps, diarrhea, flatulence, increased peristalsis

Renal and Urinary Disorders: Urinary frequency

Musculoskeletal and Connective Tissue Disorders: Arthralgia, muscle cramps, spasms, weakness

7 DRUG INTERACTIONS

The pharmacokinetic interaction between neostigmine methylsulfate and other drugs has not been studied. Neostigmine methylsulfate is metabolized by microsomal enzymes in the liver. Closely monitor patients for a longer period of time when using Neostigmine Methylsulfate Injection with other drugs which may alter the activity of metabolizing enzymes or transporters.

7.1 Depolarizing Muscle Relaxants

Use of neostigmine to reverse the effects of depolarizing muscle relaxants such as succinylcholine is not recommended, because it may prolong the phase-1 block.

7.2 Antibiotics

Certain antibiotics, particularly neomycin, streptomycin and kanamycin have nondepolarizing neuromuscular blocking action, and therefore, neostigmine dose adjustments may be required to reverse neuromuscular block in patients who have been taking these drugs. There was no effect on neostigmine action on rocuronium reversal by cefuroxime, metronidazole, cefuroxime or metronidazole.

8 USE IN SPECIFIC POPULATIONS

8.1 Pregnancy

Risk Summary

There are no adequate or well-controlled studies of Neostigmine Methylsulfate Injection in pregnant women. It is not known whether Neostigmine Methylsulfate Injection can cause fetal harm when administered to a pregnant woman or can affect reproductive capacity. The incidence of malformations in human pregnancies has not been established for neostigmine as the data are limited. All pregnancies, regardless of drug exposure, have a background risk of 2 to 4% for major birth defects, and 15 to 20% for pregnancy loss.

No adverse effects were noted in rats or rabbits treated with human equivalent doses of neostigmine methylsulfate doses up to 8.1 and 13 mcg/kg/day, respectively, during organogenesis (0.1 to 0.2-times the maximum recommended human dose of 5 mg/60 kg person/day based on body surface area comparisons).

Anticholinesterase drugs, including neostigmine may cause uterine irritability and induce premature labor when administered to pregnant women near term.

Neostigmine Methylsulfate Injection should be given to a pregnant woman only if clearly needed.

Data

Animal Data

In embryofetal development studies, rats and rabbits were administered neostigmine methylsulfate at human equivalent doses (HED, on a mg/m^2 basis) of 1.6, 4 and 8.1 mcg/kg/day 3.2, 8.1, and

13 mcg/kg/day, respectively, during the period of organogenesis (Gestation Days 6 through 17 for rats and Gestation Days 6 through 18 for rabbits). There was no evidence for a teratogenic effect in rats and rabbits up to HED 8.1 and 13 mcg/kg/day, which are approximately 0.097-times and 0.16-times the MRHD of 5 mg/60 kg, respectively in the presence of minimal maternal toxicity (tremors, ataxia, and prostration). The studies resulted in exposures in the animals well below predicted exposures in humans.

In a pre- and postnatal development study in rats, neostigmine methylsulfate was administered to pregnant female rats at human equivalent doses (HED) of 1.6, 4 and 8.1 mcg/kg/day from Day 6 of gestation through Day 20 of lactation, with weaning on Day 21. There were no adverse effects on physical development, behavior, learning ability, or fertility in the offspring occurred at HED doses up 8.1 mcg/kg/day which is 0.097-times the MRHD of 5 mg/60 kg on a mg/m^2 basis in the presence of minimal maternal toxicity (tremors, ataxia, and prostration). The studies resulted in exposures in the animals well below predicted exposures in humans.

8.2 Lactation

It is not known whether Neostigmine Methylsulfate Injection is excreted in human milk. Because many drugs are excreted in human milk and because of the potential for serious adverse reactions from Neostigmine Methylsulfate Injection in nursing infants, a decision should be made whether to discontinue nursing or to discontinue the drug, taking into account the importance of the drug to the mother.

8.4 Pediatric Use

Data from published literature support the intravenous use of neostigmine methylsulfate for reversal of nondepolarizing neuromuscular blocking agents in all pediatric age groups.

Recovery of neuromuscular activity occurs more rapidly with smaller doses of cholinesterase inhibitors in infants and children than in adults. However, infants and small children may be at greater risk of complications from incomplete reversal of neuromuscular blockade due to decreased respiratory reserve. The risks associated with incomplete reversal outweigh any risk from giving higher doses of Neostigmine Methylsulfate (up to 0.07 mg/kg or up to a total of 5 mg, whichever is lower).

The dose of Neostigmine Methylsulfate required to reverse neuromuscular blockade in children varies between 0.03 mg to 0.07 mg/kg, the same dose range shown to be effective in adults, and should be selected using the same criteria as used for adult patients [ see Clinical Pharmacology (12.3)].

Since the blood pressure in pediatric patients, particularly infants and neonates is sensitive to changes in heart rate, the effects of an anticholinergic agent (e.g., atropine) should be observed prior to administration of neostigmine to lessen the probability of bradycardia and hypotension.

8.5 Geriatric Use

Elderly patients are likely to have decreased renal function, which may prolong the duration of action of neostigmine methylsulfate. However, elderly patients also experience slower spontaneous recovery from neuromuscular blocking agents. Therefore, dosage adjustments are generally not needed in geriatric patients; however, they should be monitored for longer periods than younger adults to assure additional doses of Neostigmine Methylsulfate Injection are not required. The duration of monitoring should be predicated on the anticipated duration of action for the neuromuscular blocking agents used on the patient.

8.6 Renal Impairment

Elimination half-life of neostigmine was prolonged in anephric patients compared to normal subjects, so neostigmine concentration may increase in patients with impaired renal functions. Although no adjustments to Neostigmine Methylsulfate Injection dosing appear to be warranted in patients with impaired renal function, they should be closely monitored for a longer period of time.

To assure the effects of the neuromuscular blocking agent, particularly one cleared by the kidneys, do not persist beyond those of Neostigmine Methylsulfate Injection, the interval for re‐dosing the neuromuscular blocking agent during the surgical procedure may be useful in determining whether, and to what extent, post‐operative monitoring needs to be extended.

8.7 Hepatic Impairment

The pharmacokinetics of neostigmine methylsulfate in patients with hepatic impairment have not been studied. Neostigmine is metabolized by microsomal enzymes in the liver so neostigmine concentration may increase in patients with impaired hepatic functions. Although no adjustments to the dosing of Neostigmine Methylsulfate Injection appear to be warranted in patients with hepatic insufficiency, patients should be carefully monitored for a longer period of time.

If hepatically cleared neuromuscular blocking agents were used during the surgical procedure, their duration of action may also be prolonged by hepatic insufficiency. This could result in the effects of the neuromuscular blocking agent outlasting those of Neostigmine Methylsulfate Injection. In this regard, the interval for re-dosing the neuromuscular blocking agent during the surgical procedure may be useful in determining whether, and to what extent, post-operative monitoring needs to be extended.

10 OVERDOSAGE

Muscarinic symptoms (nausea, vomiting, diarrhea, sweating, increased bronchial and salivary secretions, and bradycardia) may appear with overdosage of neostigmine methylsulfate, but may be managed by the use of additional atropine or glycopyrrolate. The possibility of iatrogenic overdose can be lessened by carefully monitoring the muscle twitch response to peripheral nerve stimulation. Should overdosage occur, ventilation should be supported by artificial means until the adequacy of spontaneous respiration is assured, and cardiac function should be monitored.

Overdosage of neostigmine may also cause a cholinergic crisis, which is characterized by increasing muscle weakness, and through involvement of the muscles of respiration, may result in death if not promptly treated.

The treatment of an overdose of neostigmine includes immediate withdrawal of all anticholinergic medication and immediate use of atropine is also recommended. Assistance of ventilation may be required if respiration is severely depressed.

Myasthenic crisis, due to an increase in the severity of the disease, is also accompanied by extreme muscle weakness and may be difficult to distinguish from cholinergic crisis on a symptomatic basis. However, such differentiation is extremely important because increases in the dose of neostigmine methylsulfate or other drugs in this class, in the presence of cholinergic crisis or of a refractory or “insensitive” state, could have grave consequences. The two types of crises may be differentiated by the use of edrophonium chloride as well as by clinical judgment. Treatment of the two conditions differs radically. Whereas the presence of myasthenic crisis requires more intensive anticholinesterase therapy, cholinergic crisis calls for the prompt withdrawal of all drugs of this type. The immediate use of atropine in cholinergic crisis is also recommended. Atropine may also be used to lessen gastrointestinal side effects or other muscarinic reactions; but such use, by masking signs of overdosage, can lead to inadvertent induction of cholinergic crisis.

11 DESCRIPTION

Neostigmine Methylsulfate Injection, a cholinesterase inhibitor, has an empirical formula of C13H22N2O6S, a molecular weight of 334.39 g/mol and the following structural formula:

Neostigmine Methylsulfate Injection is formulated with neostigmine methylsulfate, a white crystalline powder, chemically designated as (m-hydroxyphenyl) trimethylammonium methylsulfate dimethylcarbamate.
Neostigmine Methylsulfate Injection is available in two dosage strengths; 0.5 mg/mL, and 1 mg/mL in 10 mL multiple dose amber glass vials.

The composition per mL is as follows:

Ingredients | mg/mL
Neostigmine Methylsulfate | 0.5 | 1
Phenol (as Liquefied Phenol, USP) | 4.5 | 4.5
Sodium Acetate, USP (Trihydrate) | 0.2 | 0.2
Water for Injection | q.s. | q.s

Phenol is added as a preservative. Acetic acid and/or sodium hydroxide may have been added for pH adjustment.

12 CLINICAL PHARMACOLOGY

12.1 Mechanism of Action

Neostigmine methylsulfate is a competitive cholinesterase inhibitor. By reducing the breakdown of acetylcholine, neostigmine methylsulfate induces an increase in acetylcholine in the synaptic cleft which competes for the same binding site as nondepolarizing neuromuscular blocking agents, and reverses the neuromuscular blockade.

12.2 Pharmacodynamics

Neostigmine is an anticholinesterase agent, and inhibits the hydrolysis of acetylcholine by competing with acetylcholine for binding to acetylcholinesterase at sites of cholinergic transmission. By reducing the breakdown of acetylcholine, neuromuscular transmission is facilitated. Neostigmine also has direct postsynaptic cholinomimetic effects which can be managed clinically by the co-administration of atropine or glycopyrrolate.

12.3 Pharmacokinetics

Distribution

Protein binding of neostigmine to human serum albumin ranges from 15 to 25%. The observed volume of distribution is between 0.12 and 1.4 L/kg following intravenous injection.

Elimination

Neostigmine is metabolized by microsomal enzymes in the liver and the observed elimination half-life reported is between 24 and 113 minutes.

Metabolism

Neostigmine is metabolized by microsomal enzymes in the liver.

Excretion

The observed elimination half-life reported is between 24 and 113 minutes following intravenous injection.

Specific Populations

Pediatric Population:

After intravenous administration as a 2-minute infusion (infants 2 to 10 months old: 100 mcg/kg; children 1 to 6 years old: 70 mcg/kg), the elimination half-life for infants and children were 39 ± 5 min and 48 ± 16 min (mean ± SD), respectively. Clearance for infants and children were 13.6 ± 2.8 and 11.1 ± 2.7 mL/min/kg (mean ± SD), respectively.

Renal Impairment

Elimination half-life was prolonged in anephric patients compared to normal subjects; elimination half-life for normal, transplant and anephric patients were 79.8 ± 48.6, 104.7 ± 64 and 181 ± 54 min (mean ± SD), respectively.

Hepatic Impairment

The pharmacokinetics of neostigmine in patients with hepatic impairment has not been studied. Neostigmine is metabolized by microsomal enzymes in the liver and its concentration may increase in patients with impaired hepatic functions.

Drug Interactions

The pharmacokinetic interaction between neostigmine and other drugs has not been studied. Neostigmine concentration may increase or decrease if concomitantly used drugs inhibit or induce the activity of metabolizing enzymes or transporters, respectively.

13 NONCLINICAL TOXICOLOGY

13.1 Carcinogenesis, Mutagenesis, Impairment of Fertility

Carcinogenesis:

Long-term animal studies have not been performed to evaluate the carcinogenic potential of neostigmine methylsulfate.

Mutagenesis:

Neostigmine Methylsulfate Injection was not genotoxic in the in vitro bacterial reverse mutation assay (Ames test), in the in vitro chromosome aberration assay, or the in vivo rat micronucleus assay.

Impairment of Fertility:

In a fertility and early embryonic development study in rats, male rats were treated for 28 days prior to mating and female rats were treated for 14 days prior to mating with intravenous neostigmine methylsulfate (human equivalent doses of 1.6, 4, and 8.1 mcg/kg/day, based on body surface area). No adverse effects were reported at any dose (up to 0.1-times the MRHD of 5 mg/60 kg person based on a body surface area comparison).

14 CLINICAL STUDIES

Data from published literature support the intravenous use of neostigmine methylsulfate for reversal of nondepolarizing neuromuscular blocking agents. Randomized, spontaneous-recovery-controlled or placebo-controlled studies using similar efficacy endpoints evaluated a total of 404 adult and 80 pediatric patients undergoing various surgical procedures. Patients had reductions in their recovery time from neuromuscular blockade with neostigmine methylsulfate treatment compared to spontaneous recovery and placebo treatments.

16 HOW SUPPLIED/STORAGE AND HANDLING

Neostigmine Methylsulfate Injection is available in 10 mL multiple dose amber glass vials containing a clear, colorless solution of 0.5 mg per mL (NDC 63323-413-36) or 1 mg per mL (NDC 63323-415-36) of neostigmine methylsulfate injection supplied in packages of 10 vials.

Store at 20° to 25°C (68° to 77°F) [see USP Controlled Room Temperature] and protect from light. Store vials in tray until ready for use.

The container closure is not made with natural rubber latex.
is a registered trademark of Premier, Inc., used under license.

Manufactured by:
Fresenius Kabi
Lake Zurich, IL 60047
www.fresenius-kabi.us
451471
Issued: September 2015

PACKAGE LABEL

PACKAGE LABEL - PRINCIPAL DISPLAY - Neostigmine 10 mL Vial Label
Neostigmine Methylsulfate Injection, USP
5 mg per 10 mL
(0.5 mg per mL)
For intravenous use.
10 mL Multiple Dose Vial Rx only

PACKAGE LABEL - PRINCIPAL DISPLAY - Neostigmine 10 mL Vial Tray Label
Neostigmine Methylsulfate Injection, USP
5 mg per 10 mL
(0.5 mg per mL)
For intravenous use.
10 x 10 mL
Multiple Dose Vials Rx only

PACKAGE LABEL - PRINCIPAL DISPLAY - Neostigmine 10 mL Vial Label
Neostigmine Methylsulfate Injection, USP
10 mg per 10 mL
(1 mg per mL)
For intravenous use.
10 mL Multiple Dose Vial Rx only

PACKAGE LABEL - PRINCIPAL DISPLAY - Neostigmine 10 mL Vial Tray Label
Neostigmine Methylsulfate Injection, USP
10 mg per 10 mL
(1 mg per mL)
For intravenous use.
10 x 10 mL
Multiple Dose Vials Rx only